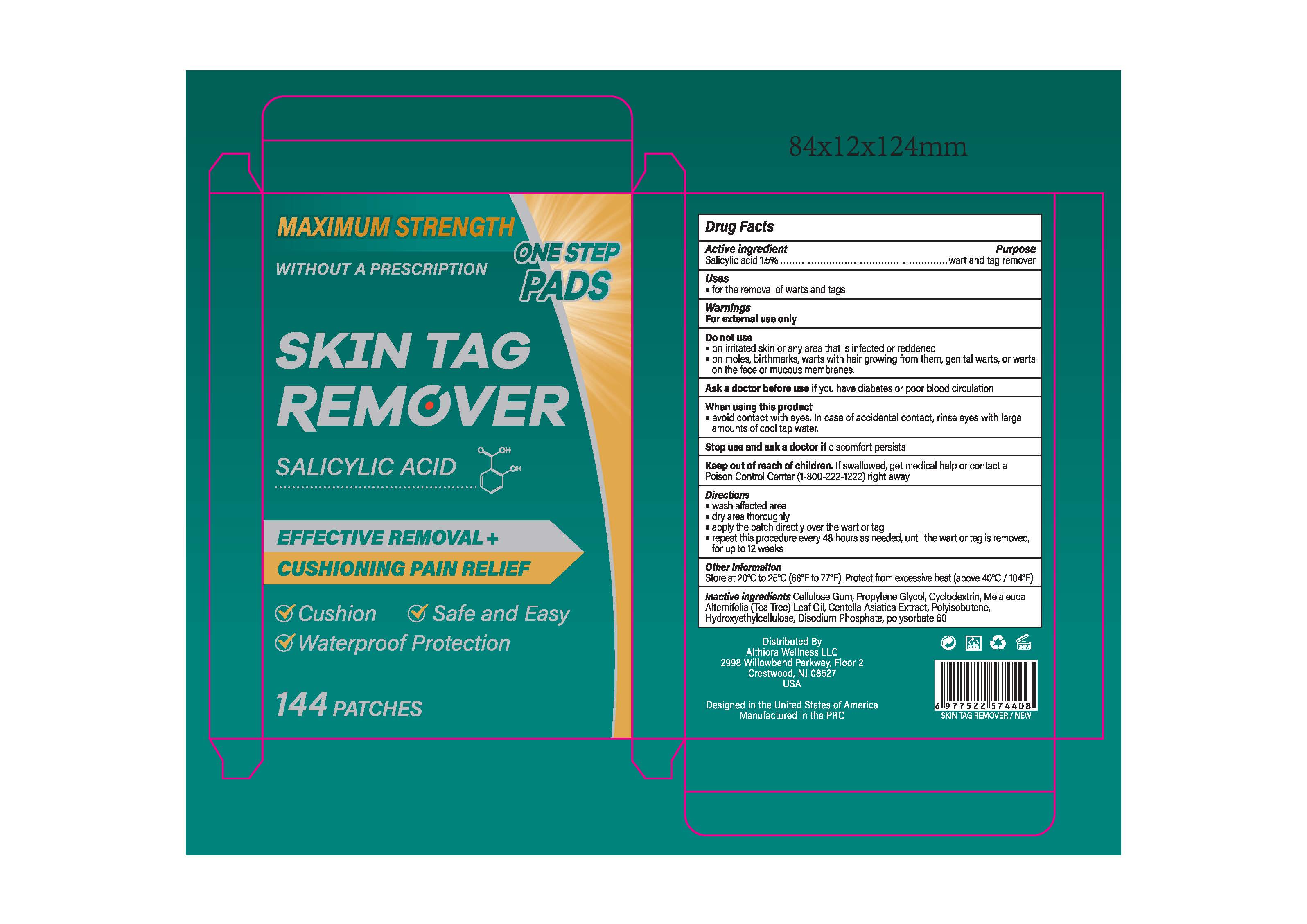 DRUG LABEL: SKIN TAG REMOVER
NDC: 85593-120 | Form: PATCH
Manufacturer: Guangzhou ChuanMa International Trading Co.,Ltd.
Category: otc | Type: HUMAN OTC DRUG LABEL
Date: 20251114

ACTIVE INGREDIENTS: SALICYLIC ACID 15 mg/1 g
INACTIVE INGREDIENTS: DISODIUM PHOSPHATE; CYCLODEXTRIN; CENTELLA ASIATICA; PROPYLENE GLYCOL; CELLULOSE GUM; HYDROXYETHYLCELLULOSE; POLYISOBUTYLENE (1300 MW); POLYSORBATE 60; MELALEUCA ALTERNIFOLIA (TEA TREE) LEAF OIL

ACTIVE INGREDIENT

Salicylic acid

PURPOSE

for the removal of warts and tags

Keep out of reach of children, lf swallowed, get medical help or contact aPoison Control Center(1-800-222-1222)right away.

WARNINGS

For external use only

DOSAGE AND ADMINISTRATION

apply the patch directly over the wart or tag

repeat this procedure every 48 hours as needed, until the wart or tag is removedfor up to 12 weeks

INDICATIONS AND USAGE

wash affected areadry area thoroughlyapply the patch directly over the wart or tagrepeat this procedure every 48 hours as needed, until the wart or tag is removed,for up to 12 weeks

INACTIVE INGREDIENT

Inactive ingredients Cellulose Gum, Propylene Glycol, Cyclodextrin, MelaleucaAlternifolia (Tea Tree) Leaf Oil, Centella Asiatica Extract, Polyisobutene,Hydroxyethylcellulose, Disodium Phosphate, polysorbate 60